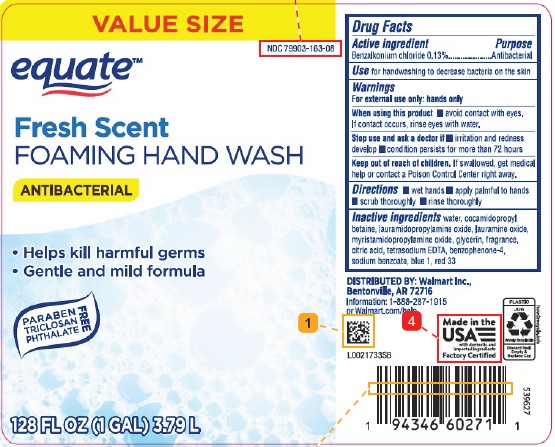 DRUG LABEL: Hand Wash
NDC: 79903-163 | Form: LIQUID
Manufacturer: Walmart Inc.
Category: otc | Type: HUMAN OTC DRUG LABEL
Date: 20260217

ACTIVE INGREDIENTS: BENZALKONIUM CHLORIDE 1.3 mg/1 mL
INACTIVE INGREDIENTS: WATER; COCAMIDOPROPYL BETAINE; LAURAMIDOPROPYLAMINE OXIDE; LAURAMINE OXIDE; MYRISTAMIDOPROPYLAMINE OXIDE; GLYCERIN; CITRIC ACID MONOHYDRATE; EDETATE SODIUM; SULISOBENZONE; SODIUM BENZOATE; FD&C BLUE NO. 1; D&C RED NO. 33

Eqaute 628.002/628AD-AF
Antibacterial Foaming Hand Wash

Active ingredient

Benzalkonium chloride 0.13%

Purpose

Antibacterial

Use

for handwashing to decrease bacteria on the skin

Warnings

For external use only: hands only

When using this product

- avoid contact with eyes. If contact occurs, rinse eyes with water.

Stop use and ask a doctor if

- irritation and redness develop
- condition persists for more than 72 hours

Keep out of reach of children.

If swallowed, get medical help or contact a Poison Control Center right away.

Directions

- wet hands
- apply palmful to hands
- scrub thoroughly
- rinse thoroughly

Inactive ingredients

water, cocamidopropyl betaine, lauramidopropylamine oxide, lauramine oxide, myristamidopropylamine oxide, glycerin, fragrance, citric acid, tetrasodium EDTA, benzophenone-4, sodium benzoate, blue 1, red 33

Adverse reaction

Distributed by: Walmart Inc.,

Bentonville, AR 72716

Information: 1-888-287-1915 or Walmart.com/help

Made in the USA with domestic and imported ingredients

Factory Certified

PLASTIC JUG

Widely Recyclable

Discard Seal, Empty & Replace Cap

how2recycle.info

Principal display panel

VALUE SIZE

NDC 79903-163-08

equate™

Fresh Scent

FOAMING HAND WASH

ANTIBACTERIAL

- Helps kill harmful germs
- Gentle and mild formula

PARABEN, TRICLOSAN, PHTHALATE FREE

128 FL OZ (1 GAL) 3.79 L